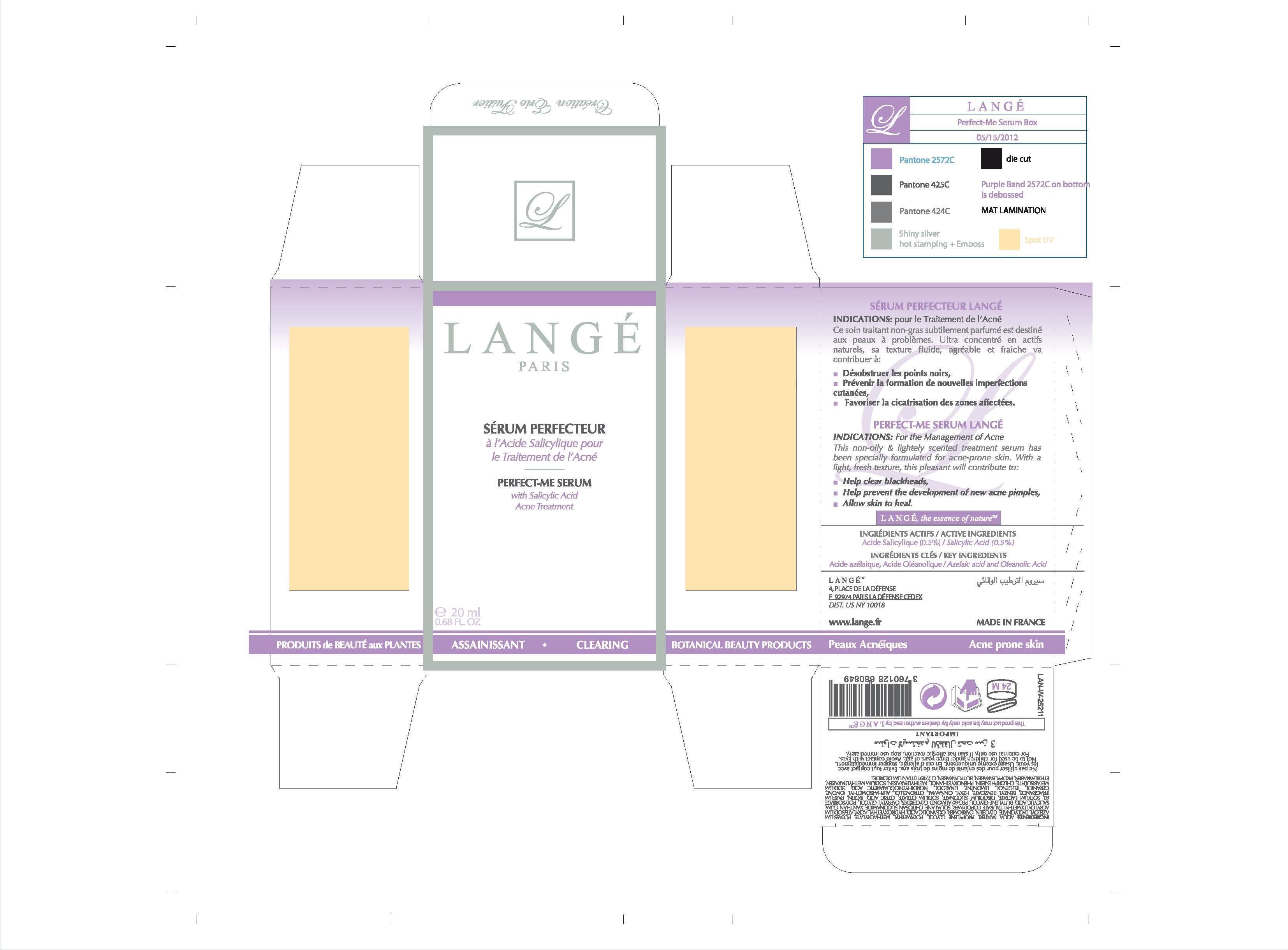 DRUG LABEL: Perfect Me Serum
NDC: 51830-052 | Form: CREAM
Manufacturer: Lange SAS
Category: otc | Type: HUMAN OTC DRUG LABEL
Date: 20130212

ACTIVE INGREDIENTS: SALICYLIC ACID 1 mg/20 mg
INACTIVE INGREDIENTS: WATER; PROPYLENE GLYCOL; POTASSIUM AZELOYL DIGLYCINATE; GLYCERIN; OLEANOLIC ACID; HYDROXYETHYL ACRYLATE/SODIUM ACRYLOYLDIMETHYL TAURATE COPOLYMER (45000 MPA.S AT 1%); SQUALANE; XANTHAN GUM; BUTYLENE GLYCOL; PEG-60 ALMOND GLYCERIDES; CAPRYLYL GLYCOL; POLYSORBATE 60; SODIUM LACTATE; SODIUM SUCCINATE ANHYDROUS; SODIUM CITRATE; CITRIC ACID MONOHYDRATE; BIOTIN; BENZYL BENZOATE; .ALPHA.-HEXYLCINNAMALDEHYDE; .BETA.-CITRONELLOL, (R)-; ISOMETHYL-.ALPHA.-IONONE; GERANIOL; EUGENOL; LINALOOL, (+)-; MASOPROCOL; SODIUM METABISULFITE; CHLORPHENESIN; PHENOXYETHANOL; METHYLPARABEN; METHYLPARABEN SODIUM; BUTYLPARABEN; ETHYLPARABEN; PROPYLPARABEN; ISOBUTYLPARABEN; TITANIUM DIOXIDE

ACTIVE INGREDIENTS
Salicyclic Acid (0.5%)
KEY INGREDIENTS
Azelaic Acid and Oleanolic Acid

PURPOSE

PERFECT-ME SERUM
with Salicyclic Acid
Acne Treatment

Keep out of reach of children.

INDICATIONS AND USAGE

PERFECT-ME SERUM LANGE
INDICATIONS: For the Management of Acne
This non-oily and lightely scented treatment serum has been specially formulated for acne-prone skin. With a light, fresh texture, this pleasant will contribute to:
Help clear blackheads,
Help prevent the development of new acne pimples,
Allow skin to heal.

WARNINGS

Not to be used for children under three years of age. Avoid contact with Eyes.
For external use only. If skin has allergic reaction, stop use immediately.

DOSAGE AND ADMINISTRATION

20 ml
0.68 FL. OZ

INACTIVE INGREDIENT

WATER
PROPYLENE GLYCOL
POLYMETHYL METHACRYLATE
POTASSIUM AZELOYL DIGLYCINATE
GLYCERIN
CARBOMER
OLEANOLIC ACID
HYDROXYETHYL ACRYLATE/SODIUM
ACRYLOYLDIMETHYLTAURATE
COPOLYMER
SQUALANE
CHITOSAN SUCCINAMIDE
XANTHAN GUM
SALICYLIC ACID
BUTYLENE GLYCOL
PEG-60 ALMOND GLYCERIDES
CAPRYLYL GLYCOL
POLYSORBATE 60
SODIUM LACTATE
DISODIUM SUCCINATE
SODIUM CITRATE
CITRIC ACID
BIOTIN
BENZYL BENZOATE
HEXYL CINNAMAL
CITRONELLOL
ALPHA-ISOMETHYL IONONE
GERANIOL
EUGENOL
LIMONENE
LINALOOL
NORDIHYDROGUAIARETIC ACID
SODIUM METABISULFITE
CHLORPHENESIN
PHENOXYETHANOL
METHYLPARABEN
SODIUM METHYLPARABEN
BUTYLPARABEN
ETHYLPARABEN
PROPYLPARABEN
ISOBUTYLPARABEN
CI 77891 (TITANIUM DIOXIDE)